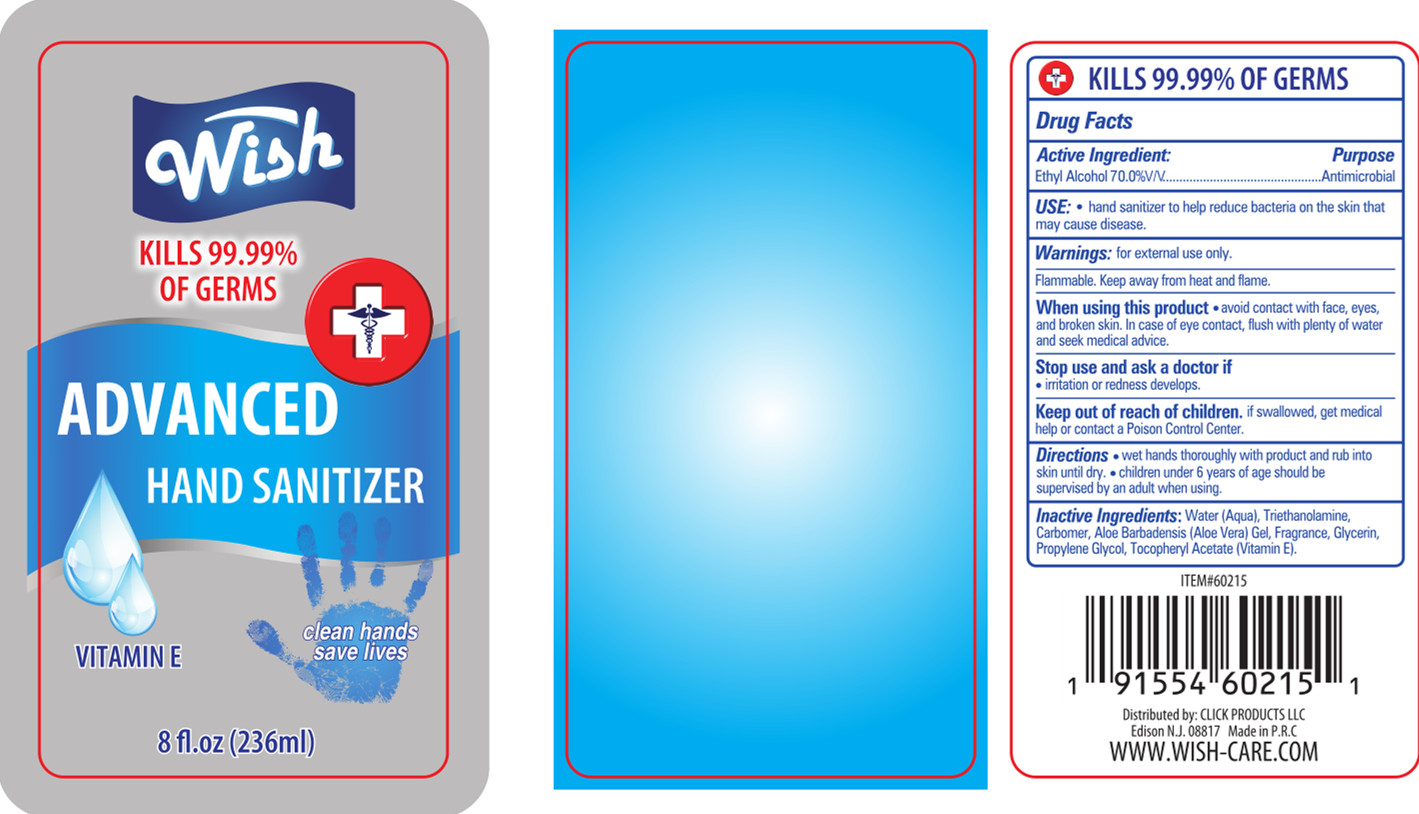 DRUG LABEL: Wish Hand Sanitizer
NDC: 54368-002 | Form: GEL
Manufacturer: YIWU ZHUDI IMPORT & EXPORT CO., LTD
Category: otc | Type: HUMAN OTC DRUG LABEL
Date: 20200426

ACTIVE INGREDIENTS: ALCOHOL 146.32 mL/236 mL
INACTIVE INGREDIENTS: ALOE VERA LEAF; GLYCERIN; CARBOMER COPOLYMER TYPE A (ALLYL PENTAERYTHRITOL CROSSLINKED); TROLAMINE; .ALPHA.-TOCOPHEROL ACETATE; FRAGRANCE LAVENDER & CHIA F-153480; PROPYLENE GLYCOL; WATER

DOSAGE AND ADMINISTRATION

Keep away from heat and flame.

INACTIVE INGREDIENT

Water

triethanolamine

carbomer

Aloe barbadensis gel

Fragrance,

glycerin

Propylene glycol

Tocopheryl acetate,

INDICATIONS AND USAGE

wet hands thoroughly with product and rub into skin until dry.

ACTIVE INGREDIENT

Ethyl Alcohol

keep out of children

PURPOSE

Disinfection
Sterilization
No Rinseing

WARNINGS

for extemnal use only.Flammable. Keep away from heat and flame.When using this product avoid contact with face, eyes,and broken skin.